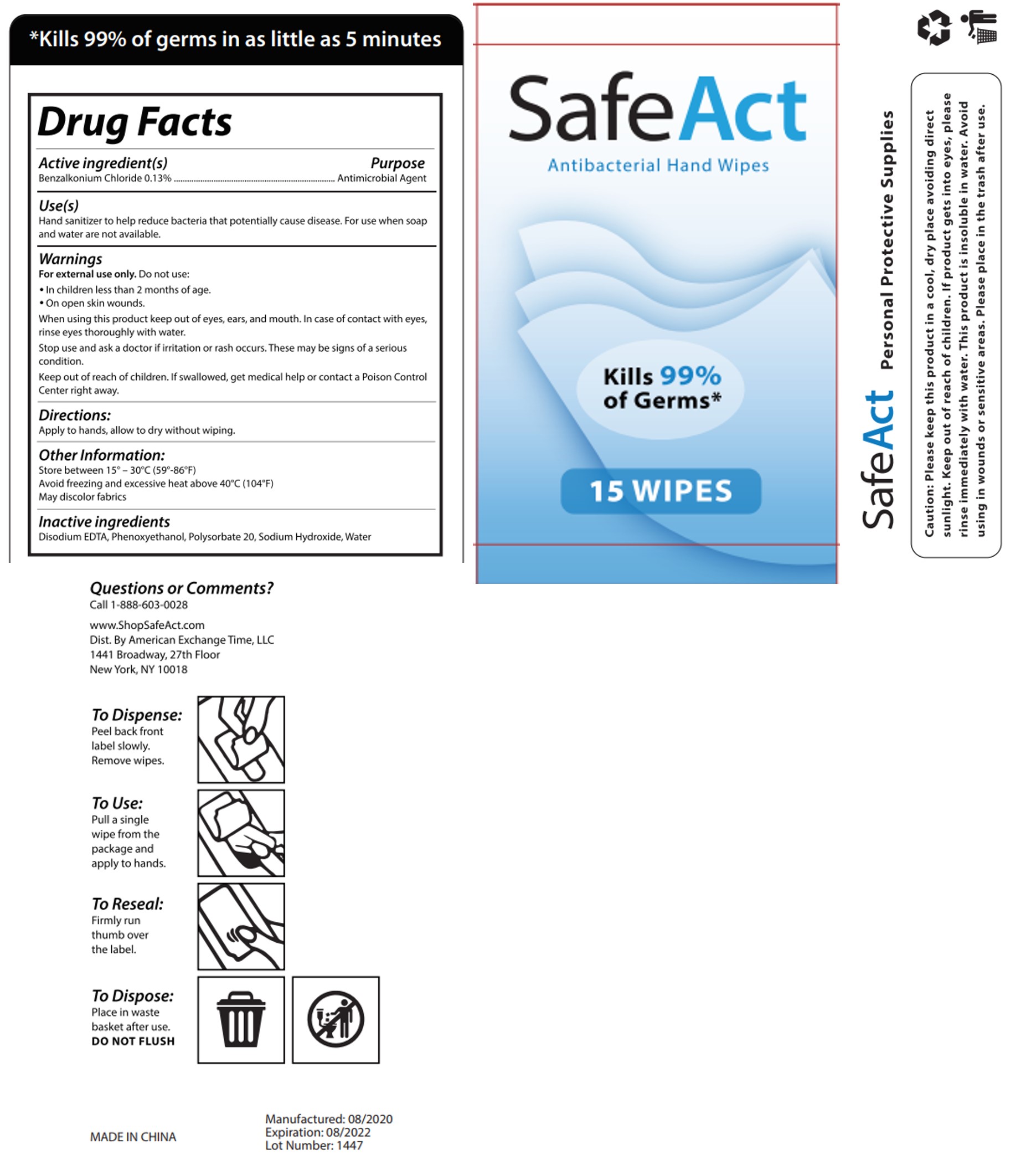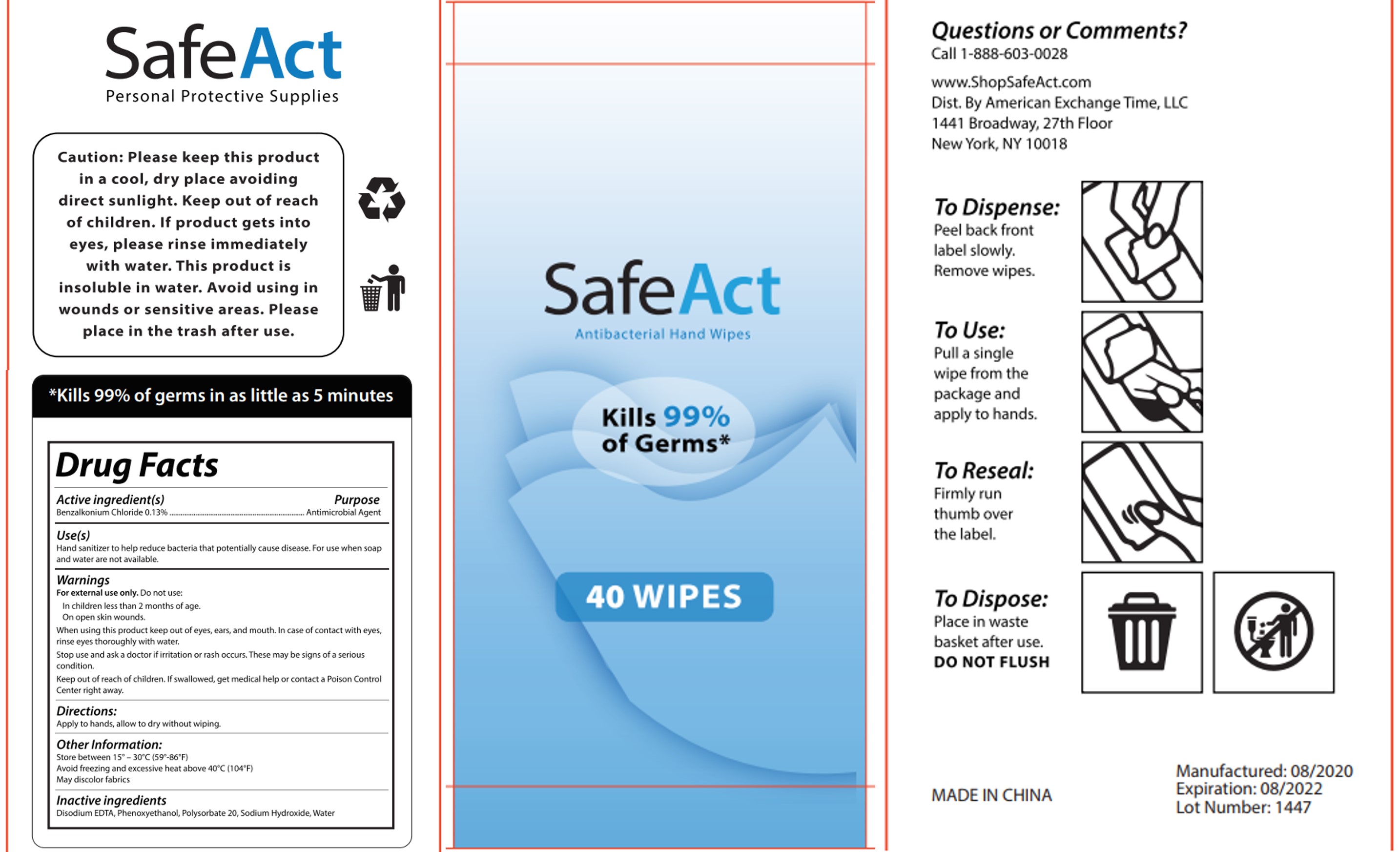 DRUG LABEL: Antibacterial Hand Wipes
NDC: 78870-002 | Form: CLOTH
Manufacturer: American Exchange Time Llc
Category: otc | Type: HUMAN OTC DRUG LABEL
Date: 20200814

ACTIVE INGREDIENTS: BENZALKONIUM CHLORIDE 0.13 g/100 g
INACTIVE INGREDIENTS: PHENOXYETHANOL 0.5 g/100 g; SODIUM HYDROXIDE 0.001 g/100 g; POLYSORBATE 20 0.05 g/100 g; WATER 99.269 g/100 g; EDETATE DISODIUM 0.05 g/100 g

Active Ingredient(s)

Benzalkonium Chloride 0.13% w/w. Purpose: Antiseptic

Purpose

Antiseptic, Hand Sanitizer

Use

Hand Sanitizer to help reduce bacteria that potentially can cause disease. For use when soap and water are not available.

Warnings

For external use only. Flammable. Keep away from heat or flame

Do not use

- in children less than 2 months of age
- on open skin wounds

When using this product keep out of eyes, ears, and mouth. In case of contact with eyes, rinse eyes thoroughly with water.
Stop use and ask a doctor if irritation or rash occurs. These may be signs of a serious condition.
Keep out of reach of children. If swallowed, get medical help or contact a Poison Control Center right away.

Stop use and ask a doctor if irritation or rash occurs. These may be signs of a serious condition.

Keep out of reach of children. If swallowed, get medical help or contact a Poison Control Center right away.

Directions

- Apply to hands, allow to dry without wiping.

Other information

- Store between 15-30C (59-86F)
- Avoid freezing and excessive heat above 40C (104F)
- May discolor fabrics

Inactive ingredients

Disodium EDTA, Phenoxyethanol, Polysorbate 20, Sodium Hydroxide, Water.

Package Label - Principal Display Panel

15 Wipes in 1 BAG NDC: 78870-002-01

Package Label - Principal Display Panel

40 Wipes in 1 BAG NDC: 78870-002-02